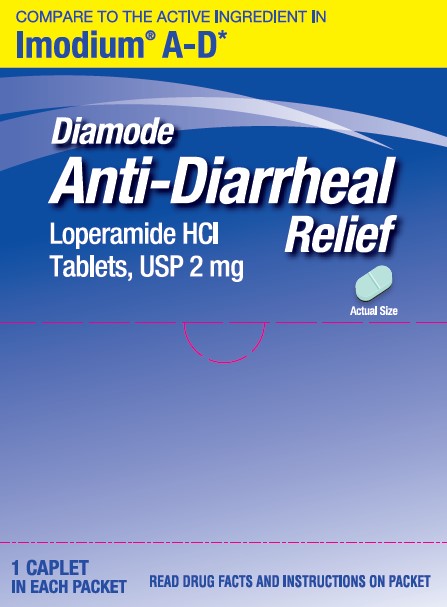 DRUG LABEL: Anti-Diarrheal
NDC: 29485-9286 | Form: TABLET
Manufacturer: Lil' Drug Store Products, Inc.
Category: otc | Type: HUMAN OTC DRUG LABEL
Date: 20241229

ACTIVE INGREDIENTS: LOPERAMIDE HYDROCHLORIDE 2 mg/1 1
INACTIVE INGREDIENTS: POWDERED CELLULOSE; D&C YELLOW NO. 10; CROSCARMELLOSE SODIUM; CROSPOVIDONE (15 MPA.S AT 5%); FD&C BLUE NO. 1; HYDROGENATED COTTONSEED OIL; MAGNESIUM STEARATE; STARCH, CORN; ANHYDROUS LACTOSE

ANTI-DIARRHEAL loperamide hcl tablet

Active Ingredient (in each tablet)

Loperamide HCl, USP 2 mg

Purpose

Anti-diarrheal

Use

Controls symptoms of diarrhea, including Travelers’ Diarrhea

Warnings

Allergy alert

Allergy alert:Do not use if you have ever had a rash or other allergic reaction to Loperamide HCl.

Heart alert

Heart alert:Taking more than directed can cause serious heart problems or death.

Do not use if you have bloody or black stool

Ask a doctor before use if you have

■ fever
■ mucus in the stool
■ a history of liver disease
■ a history of abnormal heart rhythm

Ask a doctor or pharmacist before use if you are

taking a prescription drug. Loperamide may interact with certain prescription drugs.

When using this producttiredness, drowsiness or dizziness may occur. Be careful when driving or operating machinery.

Stop use and ask a doctor if

■ symptoms get worse

■ diarrhea lasts for more than 2 days

■ you get abdominal swelling or bulging. These may be signs of a serious condition.

If pregnant or breast-feeding,

ask a health professional before use.

Keep out of reach of children.

In case of overdose, get medical help or contact a Poison Control Center right away. (1-800-222-1222)

Directions

drink plenty of clear fluids to help prevent dehydration caused by diarrhea
■ find right dose on chart. If possible, use weight to dose; otherwise use age.

adults and children 12 years and over | 2 caplets after the first loose stool;; 1 caplet after each subsequent loose stool; but no more than 4 caplets in 24 hour
children 9 - 11 years; (60 - 95 lbs) | 1 caplet after the first loose stool;; 1/2 caplet after each subsequent loose stool;; but no more than 3 caplets in 24 hours
children 6 - 8 years; (48 - 59 lbs) | 1 caplet after the first loose stool;; 1/2 caplet after each subsequent loose stool; but no more than 2 caplets in 24 hours
children 2 - 5 years; (34 - 47 lbs) | ask a doctor
children under 2; (up to 33 lbs) | do not use

Other Information

■ store between 68-77°F (20-25°C)

Inactive Ingredients

anhydrous lactose, croscarmellose sodium, crospovidone, D&C Yellow
no. 10 aluminum lake, FD&C Blue no. 1 aluminum lake, hydrogenated
vegetable oil, magnesium stearate, powdered cellulose, pregelatinized
starch

Questions or Comments?

Call 1-800-351-2000 (8:30 AM - 5:00 PM CST)

*This product is not manufactured or distributed by Johnson & Johnson Consumer Inc, McNeil Consumer Healthcare Divison, distributor of Imodium® A-D

Distributed by: Lil’ Drug Store Products, Inc., Cedar Rapids, IA 52404

2 mg Loperamide Tablet

Compare to the active ingredient in Imodium® A-D*

Diamode

Anti-Diarrheal Relief

Loperamide HCl

Tablets, USP 2 mg

[tablet image]

actual size

1 CAPLET IN EACH PACKET

READ DRUG FACTS AND INSTRUCTIONS ON PACKET